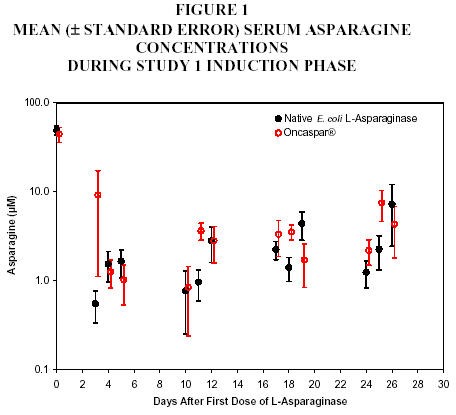 DRUG LABEL: Unknown
Category: prescription | Type: HUMAN PRESCRIPTION DRUG LABELING WITH HIGHLIGHTS
Date: 20060724

HIGHLIGHTS OF PRESCRIBING INFORMATION

RECENT MAJOR CHANGES

Indications and Usage, 9/2006
First line acute lymphoblastic leukemia (ALL) (1.1)

Contraindications, 9/2006
History of serious thrombosis with prior L-asparaginase therapy (4)

1 INDICATIONS AND USAGE

Oncaspar® is indicated as a component of a multi-agent chemotherapeutic regimen for treatment of patients with:

- First line acute lymphoblastic leukemia (1.1)
- Acute lymphoblastic leukemia and hypersensitivity to asparaginase (1.2)

2 DOSAGE AND ADMINISTRATION

- 2,500 IU/m^2 intramuscularly (IM) or intravenously (IV) no more frequently than every 14 days. (2.1)
- For IM administration, limit the volume at a single injection site to 2 mL; if greater than 2 mL, use multiple injection sites. (2.2)
- For IV administration, give over a period of 1 to 2 hours in 100 mL of sodium chloride or dextrose injection 5%, through an infusion that is already running. (2.2)
- Do not administer Oncaspar® if drug has been frozen, stored at room temperature for more than 48 hours, or shaken or vigorously agitated. (2.3)

3 DOSAGE FORMS AND STRENGTHS

- 3,750 IU/5 mL single-use vial. (3)

4 CONTRAINDICATIONS

- History of serious allergic reactions to Oncaspar®(4)
- History of serious thrombosis with prior L-asparaginase therapy (4)
- History of pancreatitis with prior L‑asparaginase therapy (4)
- History of serious hemorrhagic events with prior L-asparaginase therapy (4)

5 WARNINGS AND PRECAUTIONS

- If the following occur - discontinue Oncaspar®:
  Anaphylaxis or serious allergic reactions (5.1)
  Thrombosis (5.2)
  Pancreatitis (5.3)
- Glucose intolerance, in some cases irreversible, can occur (5.4)
- Coagulopathy can occur. Perform appropriate monitoring. (5.5)

6 ADVERSE REACTIONS

Most common adverse reactions (≥ 2%) are allergic reactions (including anaphylaxis), central nervous system (CNS) thrombosis, coagulopathy, elevated transaminases, hyperbilirubinemia, hyperglycemia, and pancreatitis. (6)

FULL PRESCRIBING INFORMATION

1 INDICATIONS AND USAGE

1.1 First Line Acute Lymphoblastic Leukemia (ALL)

Oncaspar® is indicated as a component of a multi-agent chemotherapeutic regimen for the first line treatment of patients with ALL.

1.2 Acute Lymphoblastic Leukemia and Hypersensitivity to Asparaginase

Oncaspar® is indicated as a component of a multi-agent chemotherapeutic regimen for the treatment of patients with ALL and hypersensitivity to native forms of L-asparaginase.

2 DOSAGE AND ADMINISTRATION

2.1 Recommended Dose

The recommended dose of Oncaspar® is 2,500 IU/m^2 intramuscularly (IM) or intravenously (IV). Oncaspar® should be administered no more frequently than every 14 days.

2.2 Instructions for Administration

When Oncaspar® is administered IM, the volume at a single injection site should be limited to 2 mL. If the volume to be administered is greater than 2 mL, multiple injection sites should be used.

When administered IV, Oncaspar® should be given over a period of 1 to 2 hours in 100 mL of sodium chloride or dextrose injection 5%, through an infusion that is already running.

2.3 Preparation and Handling Precautions

Do not administer Oncaspar® if drug has been:

- frozen
- stored at room temperature (+15°C to +25°C; 59°F to 77°F) for more than 48 hours
- shaken or vigorously agitated [see How Supplied/Storage and Handling (16)]

Parenteral drug products should be inspected visually for particulate matter, cloudiness, or discoloration prior to administration, whenever solution and container permit. If any of these are present, discard the vial.

3 DOSAGE FORMS AND STRENGTHS

3,750 IU/5 mL single-use vial

4 CONTRAINDICATIONS

- History of serious allergic reactions to Oncaspar®
- History of serious thrombosis with prior L-asparaginase therapy
- History of pancreatitis with prior L‑asparaginase therapy
- History of serious hemorrhagic events with prior L-asparaginase therapy

5 WARNINGS AND PRECAUTIONS

5.1 Anaphylaxis and Serious Allergic Reactions

Serious allergic reactions can occur in patients receiving Oncaspar®. The risk of serious allergic reactions is higher in patients with known hypersensitivity to other forms of L-asparaginase. Observe patients for 1 hour after administration of Oncaspar® in a setting with resuscitation equipment and other agents necessary to treat anaphylaxis (for example, epinephrine, oxygen, intravenous steroids, antihistamines). Discontinue Oncaspar® in patients with serious allergic reactions.

5.2 Thrombosis

Serious thrombotic events, including sagittal sinus thrombosis can occur in patients receiving Oncaspar®. Discontinue Oncaspar® in patients with serious thrombotic events.

5.3 Pancreatitis

Pancreatitis can occur in patients receiving Oncaspar®. Evaluate patients with abdominal pain for evidence of pancreatitis. Discontinue Oncaspar® in patients with pancreatitis.

5.4 Glucose Intolerance

Glucose intolerance can occur in patients receiving Oncaspar®. In some cases, glucose intolerance is irreversible.

5.5 Coagulopathy

Increased prothrombin time, increased partial thromboplastin time, and hypofibrinogenemia can occur in patients receiving Oncaspar®. Monitor coagulation parameters at baseline and periodically during and after treatment. Initiate treatment with fresh-frozen plasma to replace coagulation factors in patients with severe or symptomatic coagulopathy.

6 ADVERSE REACTIONS

The following serious adverse reactions occur with Oncaspar® treatment [see Warnings and Precautions (5)]:

- Anaphylaxis and serious allergic reactions
- Serious thrombosis
- Pancreatitis
- Glucose intolerance
- Coagulopathy

The most common adverse reactions with Oncaspar® are allergic reactions (including anaphylaxis), hyperglycemia, pancreatitis, central nervous system (CNS) thrombosis, coagulopathy, hyperbilirubinemia, and elevated transaminases.

6.1 Clinical Trials Experience

Because clinical trials are conducted under widely varying conditions, the adverse reaction rates observed cannot be directly compared to rates in other clinical trials and may not reflect the rates observed in clinical practice.

First-Line ALL

The data presented below are derived from 2 studies in patients with standard-risk ALL who received Oncaspar® as a component of first-line multi-agent chemotherapy. Study 1 was a randomized (1:1), active-controlled study that enrolled 118 patients, with a median age of 4.7 years (1.1-9.9 years), of whom 54% were males and 65% White, 14% Hispanic, 8% Black, 8% Asian, and 6% other. Of the 59 patients in Study 1 who were randomized to Oncaspar®, 48 patients (81%) received all 3 planned doses of Oncaspar®, 6 (10%) received 2 doses, 4 (7%) received 1 dose, and 1 patient (2%) did not receive the assigned treatment. Study 2 is an ongoing, multi-factorial design study in which all patients received Oncaspar®as a component of various multi-agent chemotherapy regimens; interim safety data are available for 2,770 patients. Study participants had a median age of 4 years (1-10 years), and were 55% male, 68% White, 18% Hispanic, 4% Black, 3% Asian, and 7% other. Per protocol, the schedule of Oncaspar®varied by treatment arm, with intermittent doses of Oncaspar® for up to 10 months.

In Study 1, detailed safety information was collected for pre-specified adverse reactions identified as asparaginase-induced adverse reactions and for grade 3 and 4 non-hematologic adverse reactions according to the Children’s Cancer Group (CCG) Toxicity and Complication Criteria. The per-patient incidence, by treatment arm, for these selected adverse reactions occurring at a severity of grade 3 or 4 are presented in Table 1 below:

TABLE 1 STUDY 1: PER-PATIENT INCIDENCE OF SELECTED GRADE 3 AND 4 ADVERSE REACTIONS
 | Oncaspar® (n=58) | Native E. coli L‑Asparaginase (n=59)
Abnormal Liver Tests | 3 (5%) | 5 (8%)
Elevated Transaminases^1 | 2 (3%) | 4 (7%)
Hyperbilirubinemia | 1 (2%) | 1 (2%)
Hyperglycemia | 3 (5%) | 2 (3%)
Central Nervous System Thrombosis | 2 (3%) | 2 (3%)
Coagulopathy^2 | 1 (2%) | 3 (5%)
Pancreatitis | 1 (2%) | 1 (2%)
Clinical Allergic Reactions to Asparaginase | 1 (2%) | 0
^1Aspartate aminotransferase, alanine aminotransferase.
^2Prolonged prothrombin time or partial thromboplastin time; or hypofibrinogenemia.

Safety data were collected in Study 2 only for National Cancer Institute Common Toxicity Criteria (NCI CTC) version 2.0, grade 3 and 4 non-hematologic toxicities. In this study, the per-patient incidence for the following adverse reactions occurring during treatment courses in which patients received Oncaspar® were: elevated transaminases, 11%; coagulopathy, 7%; hyperglycemia, 5%; CNS thrombosis/hemorrhage, 2%; pancreatitis, 2%; clinical allergic reaction, 1%; and hyperbilirubinemia, 1%. There were 3 deaths due to pancreatitis.

Previously Treated ALL

Adverse reaction information was obtained from 5 clinical trials that enrolled a total of 174 patients with relapsed ALL who received Oncaspar® as a single agent or in combination with multi-agent chemotherapy. The toxicity profile of Oncaspar® in patients with previously treated relapsed ALL is similar to that reported above with the exception of clinical allergic reactions (see Table 2). The most common adverse reactions of Oncaspar® were clinical allergic reactions, elevated transaminases, hyperbilirubinemia, and coagulopathies. The most common serious adverse events due to Oncaspar® treatment were thrombosis (4%), hyperglycemia requiring insulin therapy (3%), and pancreatitis (1%).

6.2 Clinical Allergic Reactions

Clinical allergic reactions include the following: bronchospasm, hypotension, laryngeal edema, local erythema or swelling, systemic rash, and urticaria.

First-Line ALL

Among 58 Oncaspar®-treated patients enrolled in Study 1, clinical allergic reactions were reported in 2 patients (3%). One patient experienced a grade 1 allergic reaction and the other grade 3 hives; both occurred during the first delayed intensification phase of the study (see Table 2).

Previously Treated ALL

Among 62 patients with relapsed ALL and prior hypersensitivity reactions to asparaginase, 35 patients (56%) had a history of clinical allergic reactions to native Escherichia (E.) coli L-asparaginase, and 27 patients (44%) had history of clinical allergic reactions to both native E. coli and native Erwinia L‑asparaginase. Twenty (32%) of these 62 patients experienced clinical allergic reactions to Oncaspar® (see Table 2).

Among 112 patients with relapsed ALL with no prior hypersensitivity reactions to asparaginase, 11 patients (10%) experienced clinical allergic reactions to Oncaspar® (see Table 2).

TABLE 2 INCIDENCE OF CLINICAL ALLERGIC REACTIONS, OVERALL AND BY SEVERITY GRADE
 | Toxicity Grade, n (%)
Patient Status | 1 | 2 | 3 | 4 | Total
Previously Hypersensitive Patients (n=62) | 7 (11) | 8 (13) | 4 (6) | 1 (2) | 20 (32)
Non- Hypersensitive Patients (n=112) | 5 (4) | 4 (4) | 1 (1) | 1 (1) | 11 (10)
First Line (n=58) | 1 (2) | 0 | 1 (2) | 0 | 2 (3)

6.3 Immunogenicity

As with all therapeutic proteins, there is a potential for immunogenicity, defined as development of binding and/or neutralizing antibodies to the product.

In Study 1, Oncaspar®-treated patients were assessed for evidence of binding antibodies using an enzyme-linked immunosorbent assay (ELISA) method. The incidence of protocol-specified “high-titer” antibody formation was 2% in Induction (n=48), 10% in Delayed Intensification 1 (n=50), and 11% in Delayed Intensification 2 (n=44). There is insufficient information to determine whether the development of antibodies is associated with an increased risk of clinical allergic reactions, altered pharmacokinetics, or loss of anti‑leukemic efficacy.

The detection of antibody formation is highly dependent on the sensitivity and specificity of the assay, and the observed incidence of antibody positivity in an assay may be influenced by several factors including sample handling, concomitant medications, and underlying disease. Therefore, comparison of the incidence of antibodies to Oncaspar® with the incidence of antibodies to other products may be misleading.

7 DRUG INTERACTIONS

No formal drug interaction studies, between Oncaspar® and other drugs, have been performed.

8 USE IN SPECIFIC POPULATIONS

8.1 Pregnancy

Pregnancy Category C. Animal reproduction studies have not been conducted with Oncaspar®. It is also not known whether Oncaspar® can cause fetal harm when administered to a pregnant woman or can affect reproduction capacity. Oncaspar® should be given to a pregnant woman only if clearly needed.

8.3 Nursing Mothers

It is not known whether Oncaspar® is excreted in human milk. Because many drugs are excreted in human milk and because of the potential for serious adverse reactions in nursing infants from Oncaspar®, a decision should be made to discontinue nursing or discontinue the drug, taking into account the importance of the drug to the mother.

8.4 Pediatric Use

[see Clinical Studies (14.1)]

8.5 Geriatric Use

Clinical studies of Oncaspar® did not include sufficient numbers of subjects aged 65 years and older to determine whether they respond differently than younger subjects.

10 OVERDOSAGE

Three patients received 10,000 IU/m^2 of Oncaspar® as an intravenous infusion. One patient experienced a slight increase in liver enzymes. A second patient developed a rash 10 minutes after the start of the infusion, which was controlled with the administration of an antihistamine and by slowing down the infusion rate. A third patient did not experience any adverse reactions.

11 DESCRIPTION

Oncaspar® (pegaspargase) is a modified version of the enzyme L-asparaginase. To produce Oncaspar®, L-asparaginase is modified by covalently conjugating units of monomethoxypolyethylene glycol (PEG), molecular weight of 5,000, to the enzyme, forming the active ingredient PEG-L-asparaginase. The L‑asparaginase (L-asparagine amidohydrolase, type EC-2, EC 3.5.1.1) used in the manufacture of Oncaspar® is derived from E. coli and supplied by Ovation Pharmaceuticals (U.S. License No. 1688) under a shared manufacturing arrangement. Oncaspar® activity is expressed in International Units (IU) according to the recommendation of the International Union of Biochemistry. One IU of L-asparaginase is defined as that amount of enzyme required to generate 1 µmol of ammonia per minute at pH 7.3 and 37°C.

Oncaspar® is supplied as a clear, colorless, preservative-free, isotonic sterile solution in phosphate-buffered saline, pH 7.3. Each milliliter contains Oncaspar® 750 IU ± 20% (based on specific activity of at least 85 IU per milligram protein), 1.20 mg monobasic sodium phosphate, USP, 5.58 mg dibasic sodium phosphate, USP, and 8.50 mg sodium chloride, USP, in water for injection, USP.

12 CLINICAL PHARMACOLOGY

12.1 Mechanism of Action

The mechanism of action of Oncaspar® is thought to be based on selective killing of leukemic cells due to depletion of plasma asparagine. Some leukemic cells are unable to synthesize asparagine due to a lack of asparagine synthetase and are dependent on an exogenous source of asparagine for survival. Depletion of asparagine, which results from treatment with the enzyme L-asparaginase, kills the leukemic cells. Normal cells, however, are less affected by the depletion due to their ability to synthesize asparagine.

12.2 Pharmacodynamics

In Study 1, pharmacodynamics were assessed in 57 newly diagnosed pediatric patients with standard-risk ALL who received three IM doses of Oncaspar® (2,500 IU/m^2), one each during induction and two delayed intensification treatment phases. Pharmacodynamic activity was assessed through serial measurements of asparagine in sera (n=57) and cerebrospinal fluid (CSF) (n=50). The data for asparagine depletion are presented in CLINICAL STUDIES [seeClinical Studies (14)].

12.3 Pharmacokinetics

Pharmacokinetic assessments were based on an enzymatic assay measuring asparaginase activity. Serum pharmacokinetics were assessed in 34 newly diagnosed pediatric patients with standard-risk ALL in Study 1 following IM administration of 2,500 IU/m^2. The elimination half-life of Oncaspar® was approximately 5.8 days during the induction phase. Similar elimination half-lives were observed during Delayed Intensification 1 and Delayed Intensification 2. Concentrations greater than 0.1 IU/mL were observed in over 90% of the samples from patients treated with Oncaspar® during induction, Delayed Intensification 1, and Delayed Intensification 2 for approximately 20 days.

In 3 pharmacokinetic studies, 37 patients with relapsed ALL received Oncaspar®at 2,500 IU/m^2 IM every 2 weeks. The plasma half-life of Oncaspar® was 3.2 ± 1.8 days in 9 patients who were previously hypersensitive to native E. coli L-asparaginase and 5.7 ± 3.2 days in 28 non-hypersensitive patients. The area under the plasma concentration-time curve (AUC) was 9.5 ± 4.0 IU/mL/day in the previously hypersensitive patients and 9.8 ± 6.0 IU/mL/day in the non-hypersensitive patients.

13 NONCLINICAL TOXICOLOGY

13.1 Carcinogenesis, Mutagenesis, Impairment of Fertility

- No long-term carcinogenicity studies in animals have been performed with Oncaspar®.
- No relevant studies addressing mutagenic potential have been conducted. Oncaspar® did not exhibit a mutagenic effect when tested against Salmonella typhimurium strains in the Ames assay.
- No studies have been performed on impairment of fertility.

14 CLINICAL STUDIES

14.1 First-Line ALL

The safety and effectiveness of Oncaspar® was evaluated in an open-label, multicenter, randomized, active-controlled study (Study 1). In this study, 118 pediatric patients aged 1 to 9 years with previously untreated standard-risk ALL were randomized 1:1 to Oncaspar® or native E. coli L-asparaginase as part of combination therapy. Oncaspar® was administered IM at a dose of 2,500 IU/m^2 on Day 3 of the 4‑week induction phase and on Day 3 of each of two 8-week delayed intensification phases. Native E. coli L‑asparaginase was administered IM at a dose of 6,000 IU/m^2 three times weekly for 9 doses during induction and for 6 doses during each delayed intensification phase.

The primary determination of effectiveness was based on demonstration of similar asparagine depletion (magnitude and duration) in the Oncaspar® and native E. coli L-asparaginase arms. The protocol-specified goal was achievement of asparagine depletion to a serum concentration of ≤1 μM. The proportion of patients with this level of depletion was similar between the 2 study arms during all 3 phases of treatment at the protocol-specified time points.

In all phases of treatment, serum asparagine concentrations decreased within 4 days of the first dose of asparaginase in the treatment phase and remained low for approximately 3 weeks for both Oncaspar® and native E. coli L-asparaginase arms. Serum asparagine concentrations during the induction phase are shown in Figure 1. The patterns of serum asparagine depletion in the 2 delayed intensification phases are similar to the pattern of serum asparagine depletion in the induction phase.

Note: Oncaspar® (2,500 IU/m^2 IM) was administered on Day 3
of the 4-week induction phase. Native
E. coli L‑asparaginase (6,000 IU/m^2 IM) was
administered 3 times weekly for 9 doses during induction.

CSF asparagine concentrations were determined in 50 patients during the induction phase. CSF asparagine decreased from a mean pretreatment concentration of 3.1 µM to 1.7 µM on Day 4 ± 1 and 1.5 µM 25 ± 1 days after administration of Oncaspar®. These findings were similar to those observed in the native E. coli L-asparaginase treatment arm.

While the 3-year Event-Free Survival (EFS) for the Oncaspar®and native E. coli L‑asparaginase study arms were similar and in the range of 80%, Study 1 was not designed to evaluate for differences in EFS rates.

14.2 ALL Patients Hypersensitive to Asparaginase

The safety and effectiveness of Oncaspar® was evaluated in 4 open-label studies enrolling a total of 42 patients with multiply-relapsed, acute leukemia [39 (93%) with ALL] with a history of prior clinical allergic reaction to asparaginase. Hypersensitivity to asparaginase was defined by a history of systemic rash, urticaria, bronchospasm, laryngeal edema, hypotension, or local erythema, urticaria, or swelling, greater than 2 centimeters, for at least 10 minutes following administration of any form of native E. coli L-asparaginase. All patients received Oncaspar® at a dose of 2,000 or 2,500 IU/m^2 administered IM or IV every 14 days. Patients received Oncaspar® as a single agent or in combination with multi-agent chemotherapy. The re‑induction response rate was 50% (95% confidence interval: 35%, 65%), based upon 36% complete remissions and 14% partial remissions. These results were similar to the overall response rates reported for patients with ALL receiving second-line, native E. coli L-asparaginase-containing re-induction chemotherapy. Anti-tumor activity was also observed with single-agent Oncaspar®. Three responses (1 complete remission and 2 partial remissions) were observed in 9 adult and pediatric patients with relapsed ALL and hypersensitivity to native E. coli L‑asparaginase.

16 HOW SUPPLIED/STORAGE AND HANDLING

Dosage Form

NDC 57665-002-02

3,750 IU/5 mL single-use vial individually packaged in a carton

Storage and Handling

Keep refrigerated at +2°C to +8ºC (36°F to 46°F).

Use only one dose per vial; do not re-enter the vial. Discard unused portions. Do not save unused drug for later administration.

Do not administer Oncaspar® if the drug:

- has been frozen
- has been stored at room temperature (+15°C to +25°C; 59°F to 77°F) for more than 48 hours
- has been shaken or vigorously agitated
- is cloudy, discolored, and precipitate is present.

17 PATIENT COUNSELING INFORMATION

17.1 Serious Allergic Reactions

Patients should be informed of the possibility of serious allergic reactions, including anaphylaxis, and to immediately report any swellings or difficulty breathing.

17.2 Thrombosis

Patients should be advised to immediately report any severe headache. Arm or leg swelling, acute shortness of breath, and chest pain also should be reported immediately.

17.3 Pancreatitis

Patients should be advised to immediately report any severe abdominal pain.

17.4 Glucose Intolerance

Patients should be advised to report excessive thirst or any increase in the volume or frequency of urination.

U.S. License No. 1171